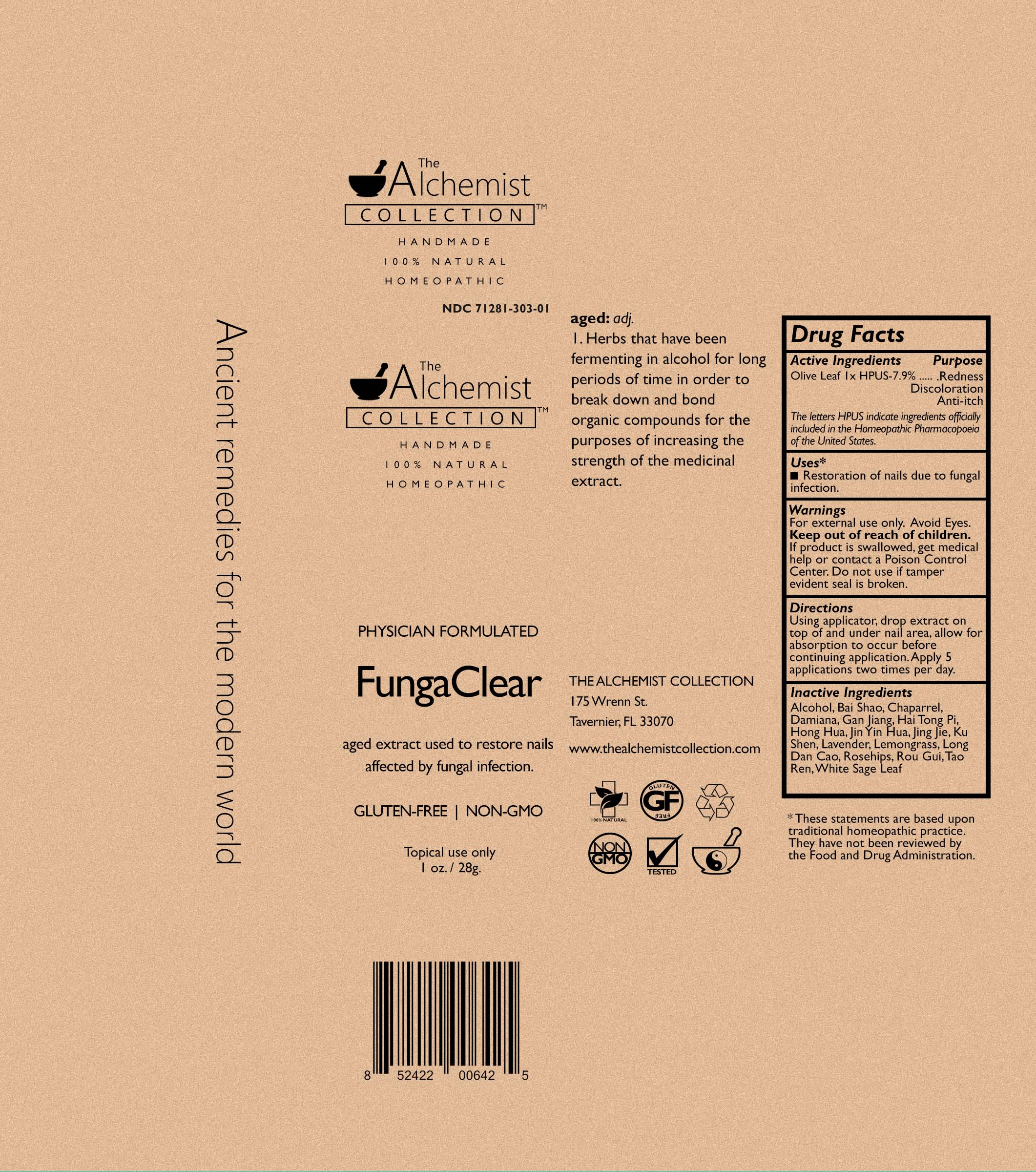 DRUG LABEL: FUNGACLEAR
NDC: 71281-303 | Form: LIQUID
Manufacturer: CANDICE NELMS, INC.
Category: homeopathic | Type: HUMAN OTC DRUG LABEL
Date: 20181219

ACTIVE INGREDIENTS: OLEA EUROPAEA LEAF 1 [hp_X]/30 mL
INACTIVE INGREDIENTS: SALVIA APIANA LEAF; SAFFLOWER; LARREA TRIDENTATA WHOLE; ROSA CANINA FRUIT; TURNERA DIFFUSA LEAFY TWIG; ERYTHRINA VARIEGATA BARK; LONICERA DASYSTYLA FLOWER BUD; NEPETA TENUIFOLIA FLOWERING TOP; SOPHORA FLAVESCENS ROOT; GINGER; EAST INDIAN LEMONGRASS OIL; GENTIANA CRASSICAULIS WHOLE; CHINESE CINNAMON; PRUNUS PERSICA SEED; LAVENDER OIL

FUNGACLEAR

Active Ingredients

Olive Leaf HPUS 1X 7.9%

Inactive Ingredients

Alcohol, Bai Shao, Chaparrel, Damiana, Gan Jiang, Hai Tong Pi, Hong Hua, Jin Yin Hua, Jing Jie, Ku Shen, Lavender, Lemongrass, Long Dan Cao, Rosehips, Rou Gui, Tao Ren, White Sage Leaf

Purpose

Active Ingredients--------Purpose
Olive Leaf .....................Redness, Discoloration, Anti-itch
The letters HPUS indicate ingredients officially included in the Homeopathic Pharmacopoeia of the United States.

Keep Out of Reach of Children

If product is swallowed, get medical help or contact a Poison Control Center.

Uses*

■ Restoration of nails due to fungal infection.

* These statements are based upon traditional homeopathic practice.
They have not been reviewed by the Food and Drug Administration.

Warnings

For external use only. Avoid Eyes.

Directions

Using applicator, drop extract on top of and under nail area, allow for absorption to occur before continuing application. Apply 5 applications two times per day.

Do not use if tamper evident seal is broken.

Aged extract to restore nails affects by fungal infection

THE ALCHEMIST COLLECTION
175 Wrenn St.
Tavernier. FL 33070
www.thealchemistcollection.com